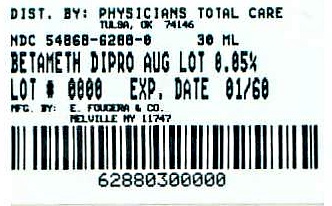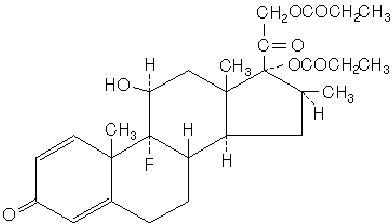 DRUG LABEL: Betamethasone Dipropionate
NDC: 54868-6288 | Form: LOTION
Manufacturer: Physicians Total Care, Inc.
Category: prescription | Type: HUMAN PRESCRIPTION DRUG LABEL
Date: 20090715

ACTIVE INGREDIENTS: betamethasone dipropionate 0.64 mg/1 mL
INACTIVE INGREDIENTS: isopropyl alcohol; propylene glycol; water; sodium phosphate, monobasic; hydroxypropyl cellulose; phosphoric acid

BETAMETHASONE DIPROPIONATE LOTION USP 0.05% (AUGMENTED*)
(potency expressed as betamethasone)
* Vehicle augments the penetration of the steroid.

FOR DERMATOLOGIC USE ONLY
NOT FOR OPHTHALMIC USE
Rx only

DESCRIPTION

Betamethasone Dipropionate Lotion USP 0.05% (Augmented) contains betamethasone dipropionate, USP, a synthetic adrenocorticosteroid, for dermatologic use. Betamethasone, an analog of prednisolone, has a high degree of corticosteroid activity and a slight degree of mineralocorticoid activity. Betamethasone dipropionate is the 17, 21-dipropionate ester of betamethasone.

Chemically, betamethasone dipropionate is 9-fluoro-11β, 17,21-trihydroxy-16β-methylpregna-1,4-diene-3,20-dione 17,21-dipropionate, with the empirical formula C28H37FO7, a molecular weight of 504.6 and the following structural formula:

It is a white to creamy-white, odorless powder insoluble in water; freely soluble in acetone and in chloroform; sparingly soluble in alcohol.

Each gram of Betamethasone Dipropionate Lotion USP 0.05% (Augmented) contains 0.643 mg betamethasone dipropionate, USP (equivalent to 0.5 mg betamethasone), in an augmented lotion base of purified water; isopropyl alcohol (30%); hydroxypropyl cellulose; propylene glycol; monobasic sodium phosphate and phosphoric acid used to adjust the pH.

CLINICAL PHARMACOLOGY

The corticosteroids are a class of compounds comprising steroid hormones secreted by the adrenal cortex and their synthetic analogs. In pharmacologic doses, corticosteroids are used primarily for their anti-inflammatory and/or immunosuppressive effects. Topical corticosteroids, such as betamethasone dipropionate, are effective in the treatment of corticosteroid-responsive dermatoses primarily because of their anti-inflammatory, antipruritic, and vasoconstrictive actions. However, while the physiologic, pharmacologic, and clinical effects of the corticosteroids are well known, the exact mechanisms of their actions in each disease are uncertain. Betamethasone dipropionate, a corticosteroid, has been shown to have topical (dermatologic) and systemic pharmacologic and metabolic effects characteristic of this class of drugs.

PHARMACOKINETICS

Pharmacokinetics: The extent of percutaneous absorption of topical corticosteroids is determined by many factors including the vehicle, the integrity of the epidermal barrier, and the use of occlusive dressings. (See DOSAGE AND ADMINISTRATION section). Topical corticosteroids can be absorbed through normal intact skin. Inflammation and/or other disease processes in the skin may increase percutaneous absorption. Occlusive dressings substantially increase the percutaneous absorption of topical corticosteroids. (See DOSAGE AND ADMINISTRATION section.) Once absorbed through the skin, topical corticosteroids enter pharmacokinetic pathways similar to systemically administered corticosteroids. Corticosteroids are bound to plasma proteins in varying degrees, are metabolized primarily in the liver and excreted by the kidneys. Some of the topical corticosteroids and their metabolites are also excreted into the bile. Studies performed with betamethasone dipropionate lotion (augmented) indicate that it is in the super-high range of potency as compared with other topical corticosteroids.

INDICATIONS AND USAGE

Betamethasone dipropionate lotion (augmented) is a super-high potency corticosteroid indicated for the relief of the inflammatory and pruritic manifestations of corticosteroid-responsive dermatoses in patients 13 years and older. The total dose should not exceed 50 mL per week because of the potential for the drug to suppress the hypothalamic-pituitary-adrenal (HPA) axis.

CONTRAINDICATIONS

Betamethasone dipropionate lotion (augmented) is contraindicated in patients who are hypersensitive to betamethasone dipropionate, to other corticosteroids, or to any ingredient in this preparation.

PRECAUTIONS

Systemic absorption of topical corticosteroids has produced reversible HPA axis suppression, manifestations of Cushing's syndrome, hyperglycemia, and glucosuria in some patients. Conditions which augment systemic absorption include the application of the more potent corticosteroids, use over large surface areas, prolonged use, and the addition of occlusive dressings. Use of more than one corticosteroid-containing product at the same time may increase total systemic glucocorticoid exposure. (See DOSAGE AND ADMINISTRATION section.)

Therefore, patients receiving a large dose of a potent topical steroid applied to a large surface area should be evaluated periodically for evidence of HPA axis suppression by using the urinary free cortisol and ACTH stimulation tests. If HPA axis suppression is noted, an attempt should be made to withdraw the drug, to reduce the frequency of application, or to substitute a less potent steroid.

Recovery of HPA axis function is generally prompt and complete upon discontinuation of the drug. Patients should not be treated with amounts of betamethasone dipropionate lotion (augmented) greater than 50 mL per week because of the potential for the drug to suppress HPA axis. Patients receiving super-potent corticosteroids should not be treated for more than 2 weeks at a time and only small areas should be treated at any one time due to the increased risk of HPA axis suppression.

Betamethasone dipropionate lotion (augmented) was applied once daily at 7 mL per day for 21 days to diseased scalp and body skin in patients with scalp psoriasis to study its effects on the HPA axis. In 2 out of 11 patients, the drug lowered plasma cortisol levels below normal limits. HPA axis suppression in these patients was transient and returned to normal within a week. In one of these patients, plasma cortisol levels returned to normal while treatment continued. Infrequently, signs and symptoms of steroid withdrawal may occur, requiring supplemental systemic corticosteroids.

Pediatric patients may absorb proportionally larger amounts of topical corticosteroids and thus be more susceptible to systemic toxicity. (See PRECAUTIONS-Pediatric Use.)

If irritation develops, topical corticosteroids should be discontinued and appropriate therapy instituted. In the presence of dermatological infections, the use of an appropriate antifungal or antibacterial agent should be instituted. If a favorable response does not occur promptly, the corticosteroid should be discontinued until the infection has been adequately controlled. Betamethasone dipropionate lotion (augmented) should not be used in the treatment of rosacea or perioral dermatitis, and it should not be used on the face, groin or in the axillae.

PATIENT COUNSELING INFORMATION

Information for Patients: Patients using topical corticosteroids should receive the following information and instructions. This information is intended to aid in the safe and effective use of this medication. It is not a disclosure of all possible adverse or intended effects.

1. This medication is to be used as directed by the physician and should not be used longer than the prescribed time period. It is for external use only. Avoid contact with the eyes.
2. This medication should not be used for any disorder other than that for which it was prescribed.
3. The treated skin area should not be bandaged, or otherwise covered or wrapped, so as to be occlusive (See DOSAGE AND ADMINISTRATION section).
4. Patients should report to their physician any signs of local adverse reactions.
5. Patients should be advised not to use betamethasone dipropionate lotion (augmented) in the treatment of diaper dermatitis. Betamethasone dipropionate lotion (augmented) should not be applied in the diaper areas as diapers or plastic pants may constitute occlusive dressing (See DOSAGE AND ADMINISTRATION).
6. This medication should not be used on the face, underarms, or groin areas unless directed by the physician.
7. As with other corticosteroids, therapy should be discontinued when control is achieved. If no improvement is seen within 2 weeks, contact the physician.
8. Other corticosteroid-containing products should not be used with betamethasone dipropionate lotion (augmented).

LABORATORY TESTS

Laboratory Tests: The following tests may be helpful in evaluating patients for HPA axis suppression: ACTH stimulation test, Urinary free cortisol test.

CARCINOGENESIS AND MUTAGENESIS AND IMPAIRMENT OF FERTILITY

Carcinogenesis, Mutagenesis, and Impairment of Fertility: Long-term animal studies have not been performed to evaluate the carcinogenic potential of betamethasone dipropionate. Betamethasone was negative in the bacterial mutagenicity assay (Salmonella typhimurium and Escherichia coli), and in the mammalian cell mutagenicity assay (CHO/HGPRT). It was positive in the in-vitro, human lymphocyte chromosome aberration assay, and equivocal in the in-vivo mouse bone marrow micronucleus assay. This pattern of response is similar to that of dexamethasone and hydrocortisone. Studies in rabbits, mice and rats using intramuscular doses up to 1, 33 and, 2, mg/kg, respectively, resulted in dose related increases in fetal resorptions in rabbits and mice.

PREGNANCY

Pregnancy: Teratogenic Effects: Pregnancy Category C. Corticosteroids have been shown to be teratogenic in laboratory animals when administered systemically at relatively low dosage levels. Some corticosteroids have been shown to be teratogenic after dermal application in laboratory animals. Betamethasone dipropionate has been shown to be teratogenic in rabbits when given by the intramuscular route at doses of 0.05 mg/kg. This dose is approximately 0.2 times the human topical dose of betamethasone dipropionate lotion (augmented) in mg/m^2 of body surface area, assuming 100% absorption and the use in a 60 kg person of 7 g per day. The abnormalities observed included umbilical hernias, cephalocele and cleft palate. There are no adequate and well-controlled studies in pregnant women on teratogenic effects from topically applied corticosteroids. Betamethasone dipropionate lotion (augmented) should be used during pregnancy only if the potential benefit justifies the potential risk to the fetus.

NURSING MOTHERS

Nursing Mothers: Systemically administered corticosteroids appear in human milk and could suppress growth, interfere with endogenous corticosteroid production, or cause other untoward effects. It is not known whether topical administration of corticosteroids could result in sufficient systemic absorption to produce detectable quantities in human milk. Because many drugs are excreted in human milk, caution should be exercised when betamethasone dipropionate lotion (augmented) is administered to a nursing woman.

PEDIATRIC USE

Pediatric Use: Use of betamethasone dipropionate lotion (augmented) in pediatric patients 12 years of age and younger is not recommended. (See CLINICAL PHARMACOLOGY and ADVERSE REACTIONS sections.) Pediatric patients may demonstrate greater susceptibility to topical corticosteroid-induced HPA axis suppression and Cushing's syndrome than mature patients because of a larger skin surface area to body weight ratio. Hypothalamic-pituitary-adrenal (HPA) axis suppression, Cushing's syndrome, and intracranial hypertension have been reported in children receiving topical corticosteroids. Manifestations of adrenal suppression in children include linear growth retardation, delayed weight gain, low plasma cortisol levels and absence of response to ACTH stimulation. Manifestations of intracranial hypertension include bulging fontanelles, headaches, and bilateral papilledema. Chronic corticosteroid therapy may interfere with the growth and development of children.

GERIATRIC USE

Geriatric Use: Seven clinical studies of betamethasone dipropionate lotion (augmented) evaluated 407 subjects or which 56 subjects were 65 years of age and over and 9 subjects were 75 years of age and over. No overall differences in safety or effectiveness were observed in these clinical studies between geriatric subjects and younger subjects. There was a numerical difference for application site reactions (most frequently reported events were burning and stinging) which occurred in 15% (10/65) of geriatric subjects and 11% (38/342) of subjects less than 65 years of age. Other reported clinical experience has not identified differences in responses between the elderly and younger patients. However, greater sensitivity of some older individuals cannot be ruled out.

ADVERSE REACTIONS

The local adverse reactions which were reported with betamethasone dipropionate lotion (augmented) during controlled clinical trials were as follows: erythema, folliculitis, pruritus and vesiculation each occurring in less than 1% of patients.

The following additional local adverse reactions have been reported with topical corticosteroids, and they may occur more frequently with the use of occlusive dressings and higher potency corticosteroids. These reactions are listed in an approximately decreasing order of occurrence: burning, itching, irritation, dryness, folliculitis, hypertrichosis, acneiform eruptions, hypopigmentation, perioral dermatitis, allergic contact dermatitis, secondary infection, skin atrophy, striae and miliaria. Systemic absorption of topical corticosteroids has produced reversible hypothalamic-pituitary-adrenal (HPA) axis suppression, manifestations of Cushing's syndrome, hyperglycemia, and glucosuria in some patients.

OVERDOSAGE

Topically applied betamethasone dipropionate lotion (augmented) can be absorbed in sufficient amounts to produce systemic effects (See PRECAUTIONS).

DOSAGE AND ADMINISTRATION

Apply a few drops of betamethasone dipropionate lotion (augmented) to the affected skin once or twice daily and massage lightly until the lotion disappears. Betamethasone dipropionate lotion (augmented) is a super-high potency topical corticosteroid. Treatment with betamethasone dipropionate lotion (augmented) should be limited to two weeks, and amounts greater than 50 mL per week should not be used. As with other highly active corticosteroids, therapy should be discontinued when control is achieved. If no improvement is seen within 2 weeks, reassessment of diagnosis may be necessary.

Betamethasone dipropionate lotion (augmented) should not be used with occlusive dressings. Betamethasone dipropionate lotion (augmented) should not be applied to the diaper area if the patient requires diapers or plastic pants as these garments may constitute occlusive dressing.

HOW SUPPLIED

Betamethasone Dipropionate Lotion USP 0.05% (Augmented) is supplied as follows:

30 mL NDC 54868-6288-0

Store at 25°C (77°F); excursions permitted to 15°-30°C (59°-86°F)[see USP Controlled Room Temperature].

E. FOUGERA & CO.
A division of Nycomed US Inc.
MELVILLE, NEW YORK 11747

I2267A
R1/08
#105

Relabeling (Additional barcode label) by:
Physicians Total Care, Inc.
Tulsa, OK 74146

PACKAGE LABEL

NDC 54868-6288-0

BETAMETHASONE
DIPROPIONATE LOTION
USP, 0.05% (AUGMENTED*)
(Potency expressed as betamethasone)
*Vehicle augments the penetration of the steroid.

For Topical Use Only.
Not for Ophthalmic Use.

Rx Only

DO NOT USE IN EYES

30 mL